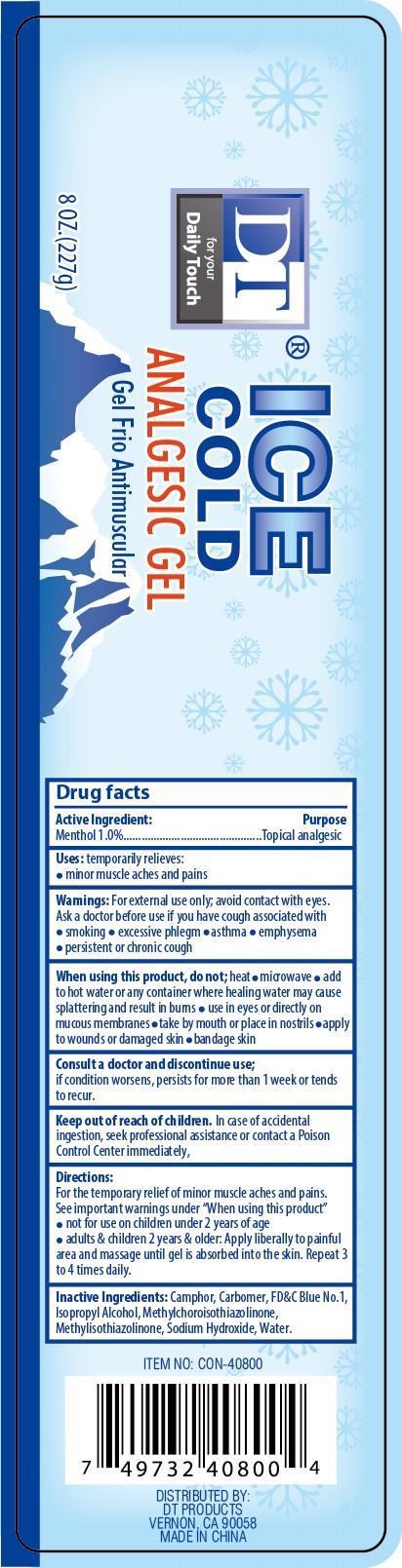 DRUG LABEL: Ice Cold Analgesic
NDC: 50523-087 | Form: GEL
Manufacturer: Volume Distributors, Inc.
Category: otc | Type: HUMAN OTC DRUG LABEL
Date: 20150710

ACTIVE INGREDIENTS: MENTHOL 1 g/100 g
INACTIVE INGREDIENTS: CAMPHOR (NATURAL); CARBOMER COPOLYMER TYPE A; FD&C BLUE NO. 1; ISOPROPYL ALCOHOL; METHYLCHLOROISOTHIAZOLINONE; METHYLISOTHIAZOLINONE; SODIUM HYDROXIDE; WATER

Active Ingredient Purpose

Menthol 1.0% ............. Topical Analgesic

PURPOSE

Uses temporarily relieves:

- minor muscle aches and pains

Keep out of reach of children. In case of accidental ingestion, seek professional assistance or contact a Poison Control Center immediately.

INDICATIONS AND USAGE

DT for your DailyTouch

Ice Cold Analgesic Gel

Gel Frio Antimuscular

Directions

For the temporary relief of minor muscle aches and pains.

See important warnings under "When using this product"

- not for use on children under 2 years of age
- adults & children 2 years & older: apply liberally to painful area and massage until gel is absorbed into the skin. Repeat 3 to 4 times daily.

Warnings

For external use only; avoid contact with eyes.

Ask a doctor before use if you have cough associated with

- smoking
- excessive phlegm
- asthma
- emphysema
- persistent or chronic cough

When using this product,do not:

- heat
- microwave
- add to hot water or any container where healing water may cause splattering and result in burns
- use in eyes or directly on mucous membranes
- take my mouth or place in nostrils
- apply to wounds or damaged skin
- bandage skin

Consult a doctor and discontinue use: if condition worsens, persists for more than 1 week or tends to recur.

Inactive Ingredients

camphor, carbomer, FD&C blue no.1, isopropyl alcohol, methylchloroisothiazolinone, methylisothiazolinone, sodium hydroxide, water.